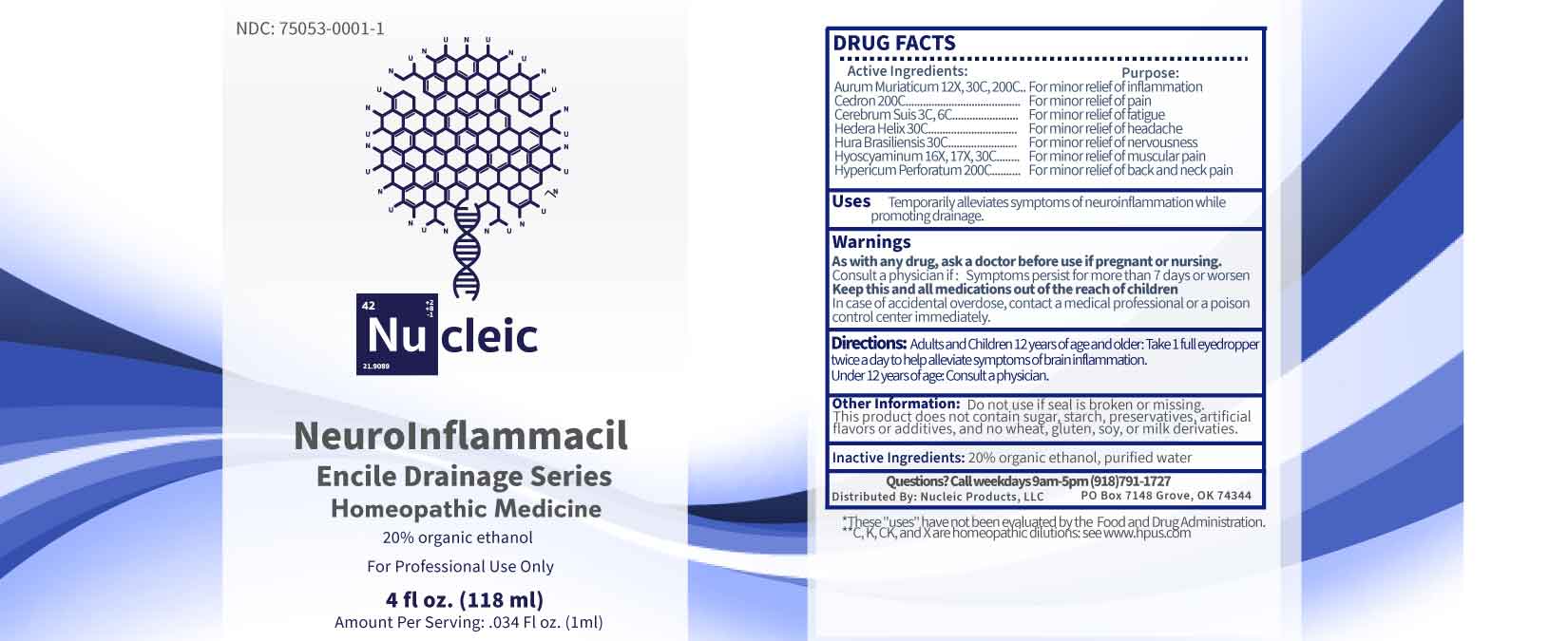 DRUG LABEL: Neuroinflammacil
NDC: 75053-0001 | Form: LIQUID
Manufacturer: Nucleic Products, LLC
Category: homeopathic | Type: HUMAN OTC DRUG LABEL
Date: 20251124

ACTIVE INGREDIENTS: GOLD TRICHLORIDE 12 [hp_X]/1 mL; HYOSCYAMINE 16 [hp_X]/1 mL; SUS SCROFA CEREBRUM 3 [hp_C]/1 mL; HEDERA HELIX FLOWERING TWIG 30 [hp_C]/1 mL; HURA CREPITANS SAP 30 [hp_C]/1 mL; SIMABA CEDRON SEED 200 [hp_C]/1 mL; HYPERICUM PERFORATUM WHOLE 200 [hp_C]/1 mL
INACTIVE INGREDIENTS: WATER; ALCOHOL

DRUG FACTS:

ACTIVE INGREDIENTS:

Aurum Muriaticum 12X, 30C, 200C, Cedron 200C, Cerebrum Suis 3C, 6C, Hedera Helix 30C, Hura Brasiliensis 30C, Hyoscyaminum 16X, 17X, 30C, Hypericum Perforatum 200C.

PURPOSE:

Aurum Muriaticum – For minor relief of inflammation, Cedron - For minor relief of pain, Cerebrum Suis - For minor relief of fatigue, Hedera Helix - For minor relief of headache, Hura Brasiliensis - For minor relief of nervousness, Hyoscyaminum - For minor relief of muscular pain, Hypericum Perforatum - For minor relief of back and neck pain.

USES:

Temporarily alleviates symptoms of neuroinflammation while promoting drainage.

*These "uses" have not been evaluated by the Food and Drug Administration.

**C, K, CK, and X are homeopathic dilutions see www.hpus.com

WARNINGS:

As with any drug, ask a doctor before use if pregnant or nursing.

Consult a physician if: Symptoms persist for more than 7 days or worsen.

Keep this and all medications out of reach of children.

In case of accidental overdose, contact a medical professional or poison control center immediately.

Do not use if seal is broken or missing.

This Product does not contain sugar, starch, preservatives, artificial flavors or additives, and no wheat, gluten, soy or milk derivatives.

KEEP OUT OF REACH OF CHILDREN:

In case of accidental overdose, contact a medical professional or poison control center immediately.

DIRECTIONS:

Adults and children 12 years of age and older: Take 1 full eyedropper twice a day to help alleviate symptoms of brain inflammation.

Under 12 years of age: Consult a physician.

INACTIVE INGREDIENTS

20% organic ethanol, purified water

QUESTIONS:

Distributed By:

Nucleic Products, LLC

PO Box 7148 Grove, OK 74344

Call weekdays 9am-5pm (918)791-1727

PACKAGE LABEL DISPLAY:

NDC: 75053-0001-1

Nu cleic

Neuroinflammacil

Homeopathic Medicine

For Professional Use Only

4 fl oz. (118 ml)